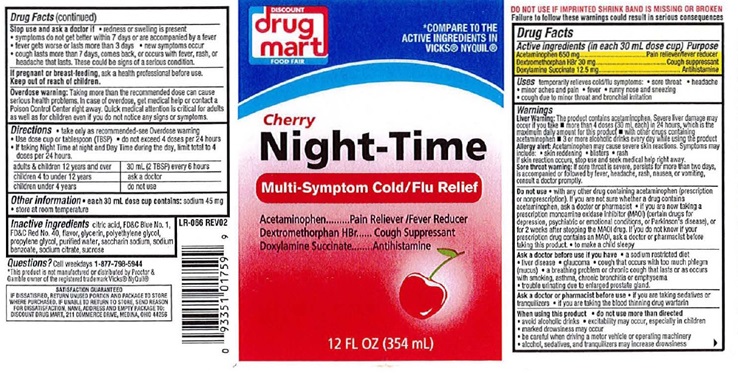 DRUG LABEL: Night-Time

NDC: 53943-502 | Form: LIQUID
Manufacturer: Discount Drug Mart
Category: otc | Type: HUMAN OTC DRUG LABEL
Date: 20251219

ACTIVE INGREDIENTS: ACETAMINOPHEN 650 mg/30 mL; DEXTROMETHORPHAN HYDROBROMIDE 30 mg/30 mL; DOXYLAMINE SUCCINATE 12.5 mg/30 mL
INACTIVE INGREDIENTS: ANHYDROUS CITRIC ACID; FD&C BLUE NO. 1; FD&C RED NO. 4; GLYCERIN; POLYETHYLENE GLYCOL, UNSPECIFIED; PROPYLENE GLYCOL; WATER; SACCHARIN SODIUM; SODIUM BENZOATE; SODIUM CITRATE; SUCROSE

Cherry Night-Time Multi-Symptom Cold/Flu Relief

Drug Facts Active ingredients (in each 30 mL dose cup)

Acetaminophen 650 mg

Dextromethorphan HBr 30 mg

Doxylamine Succinate 12.5 mg

Purpose

Pain reliver/fever reducer

Cough suppressant

Antihistamine

Uses

temporarily relieves cold/flu symptoms

- sore throat
- headache
- minor aches and pain
- fever
- runny nose and sneezing
- cough due to minor throat annd bronchial iritation

Warnings
Liver Warning:This product contains acetaminophen. Severe liver damage
may occur if you take ■ more than 4 doses in 24 hours, which is
the maximum daily amount for this product ■ with other drugs containing
acetaminophen ■ 3 or more alcoholic drinks every day while using this
product
Allery alert:Acetaminophen may cause severe skin reactions. Symptoms may
include: ● skin reddening ● blisters ● rash
If skin reaction occurs, stop use and seek medical help right away.
Sore throat warning:If sore throat is severe, persists for more than two
days, is accompanied or followed by fever, headache, rash, nausea, or vomiting,
consult a doctor promptly.

Do not use

- with any other drug containing acetaminophen (prescription or nonprescription) If you are not sure whether a drug contains acetaminophen, ask a doctor or pharmacist
- if you are now taking a prescription monamine oxidase inhibitor (MAOI) (certain drugs for depression psychiatric or emotional conditions, or Parkinson's disease), or for 2 weeks after stopping the MAOI drug. If you do not know if your prescription drug contains an MAOI, ask a doctor or pharmacist before taking this product.
- to make a child sleepy

Ask a doctor before use if you have

- a sodium restricted diet
- liver disease
- glaucoma
- cough that occurs with too much phlegm (mucus)
- a breathing problem or chronic cough that lasts or as occurs with smoking, asthma, chronic bronchitis or emphysema
- trouble urinating due to enlarged prostate gland.

Ask a doctor or pharmacist before use

- if you are taking sedatives or tranquilizers
- if you are taking the blood thinning drug warfarin.

When using this product

- do not use more than directed
- avoid alcoholic drinks
- excitability may occur, especially in children
- marked drowsiness may occur
- be careful when driving a motor vehicle or operating machinery
- alcohol, sedatives, and tranquilizers may increase drowsiness

Stop use and ask a doctor if

- redness or swelling is present
- symptoms do not get better within 7 days or are accompanied by a fever
- fever gets worse or lasts more than 3 days
- new symptoms occur
- cough lasts more than 7 days, comes back, or occurs with fever, rash, or headache that lasts. These could be signs of a serious condition.

If pregnant or breast-feeding,

ask a health professional before use.

Keep out of reach of children.

Overdose warning:

Taking more than the recommended dose can cause serious health problems. In case of overdose, get medical help, or contact a Poison Control Center right away. Quick medical attention is critical for adults as well as children even if you do not notice any signs or symptoms

Directions

- take only as recommended-see Overdose warning
- Use dose cup or tablespoon (TBSP)
- do not exceed 4 doses per 24 hours
- if taking Night Time at night and Day Time during the day, limit total to 4 doses per 24 hours.

adults and children 12 years and over | 30 mL (2TBSP) every 6 hours
children 4 to under 12 years | ask a doctor
children under 4 years | do not use

Other information

- each 30mL dose cup contains:sodium 45 mg
- store at room temperature

Inactive ingredients

citric acid, FD and C Blue No. 1, FD and C Red No. 40, flavor, glycerin, polyethylene glycol, propylene glycol, purified water, saccharin sodium, sodium benzoate, sodium citrate, sucrose

Questions?

Call weekdays 1-877-798-5944

DISCOUNT drug mart FOOD FAIR Cherry Night-Time Multi-Symptom Cold/Flu Relief product label

*COMPARE TO THE ACTIVE INGREDIENTS IN VICKS®NYQUIL®

DISCOUNT

drug mart

FOOD FAIR

Cherry

Night-Time Multi-Symptom Cold/Flu Relief

Acetaminophen ...... Pain Reliever/Fever Reducer

Dextromethorphan HBR ....... Cough Suppressant

Doxylamine Succinate ........... Antihistamine

12 FL OZ (354 mL)

* This product is not manufactured or distributed by Proctor and Gamble owner of the registered trademark Vicks® Nyquil®

LR-066 REV 01

SATISFACTION GUARANTEED

IF DISSATISFIED, RETURN UNUSED PORTION AND PACKAGE TO THE STORE WHERE PURCHASED. IF UNABLE TO RETURN TO THE STORE, SEND REASON FOR DISSATISFACTION , NAME, ADDRESS AND EMPTY PACKAGE TO: DISCOUNT DRUG MART, 211 COMMERCE DRIVE MEDINNA, OHIO 44256

res